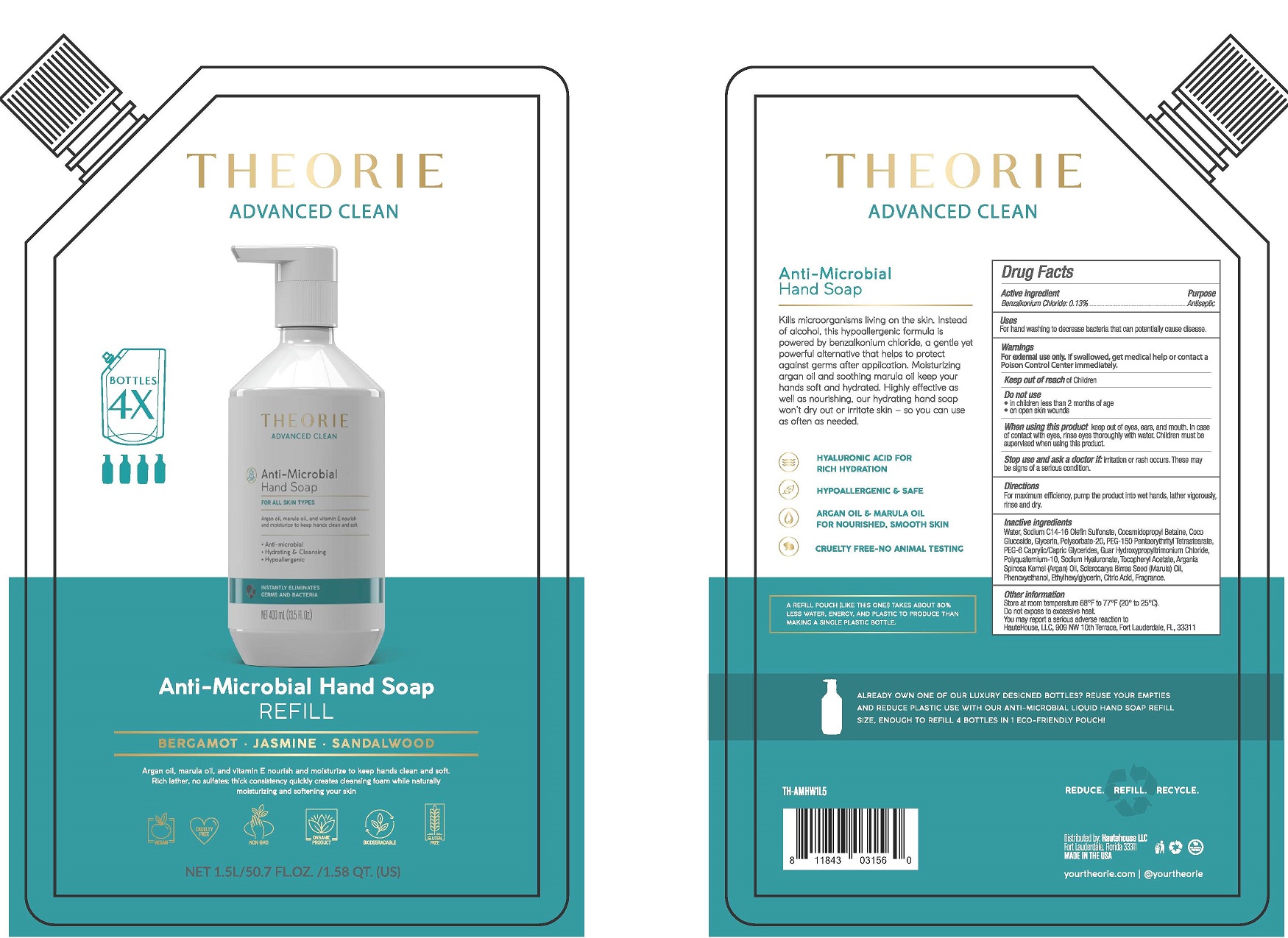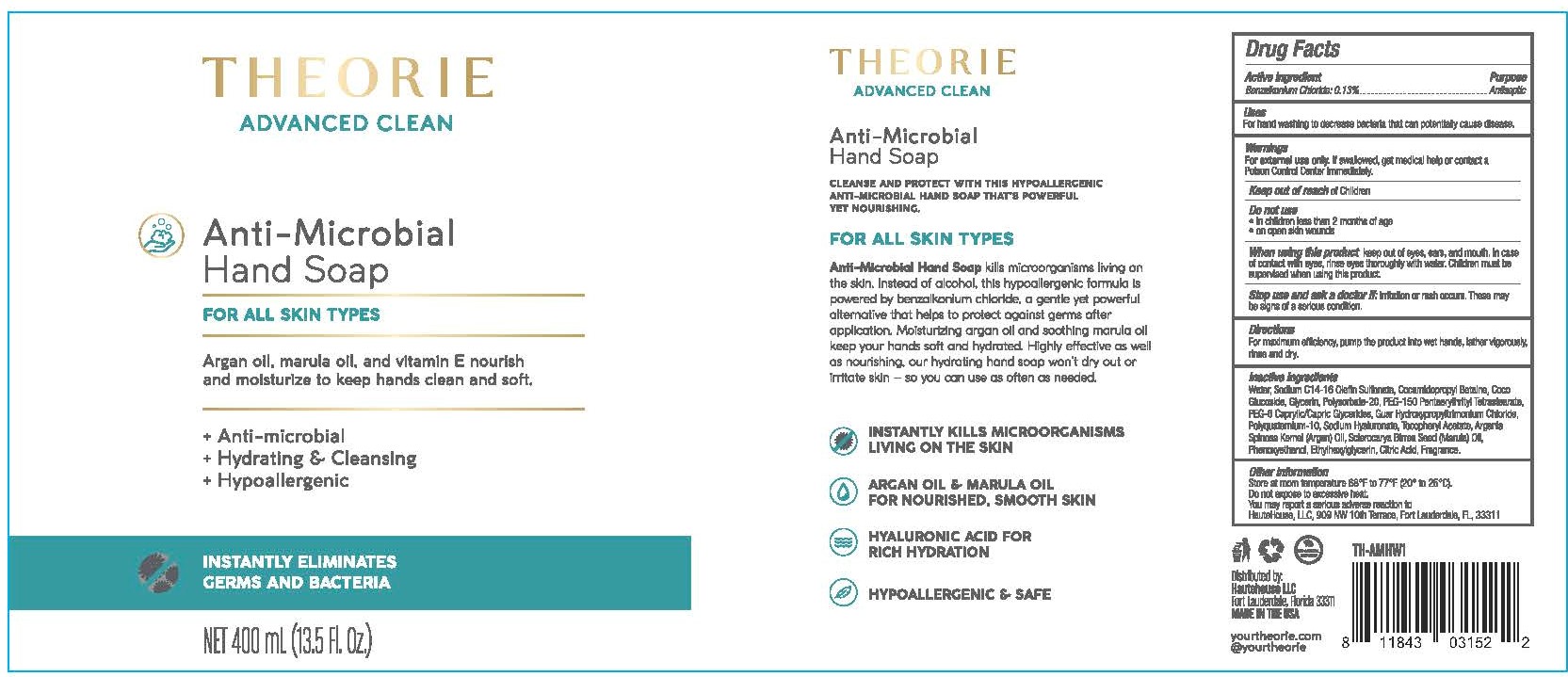 DRUG LABEL: Theorie Antimicrobial Hand WASH
NDC: 73857-003 | Form: SOAP
Manufacturer: Dynastis, LLC
Category: otc | Type: HUMAN OTC DRUG LABEL
Date: 20230111

ACTIVE INGREDIENTS: BENZALKONIUM CHLORIDE .0013 kg/1 kg
INACTIVE INGREDIENTS: WATER; SODIUM C14-16 OLEFIN SULFONATE; COCAMIDOPROPYL BETAINE; COCO GLUCOSIDE; GLYCERIN; POLYSORBATE 20; PEG-150 PENTAERYTHRITYL TETRASTEARATE; PEG-6 CAPRYLIC/CAPRIC GLYCERIDES; GUAR HYDROXYPROPYLTRIMONIUM CHLORIDE (1.7 SUBSTITUENTS PER SACCHARIDE); POLYQUATERNIUM-10 (30000 MPA.S AT 2%); HYALURONATE SODIUM; .ALPHA.-TOCOPHEROL ACETATE; ARGAN OIL; SCLEROCARYA BIRREA SEED OIL; PHENOXYETHANOL; ETHYLHEXYLGLYCERIN; CITRIC ACID MONOHYDRATE

Theorie Antimicrobial Hand Soap

DRUG FACTS

Benzalkonium Chloride 0.13%

Uses

For hand washing to decrease bacteria that can potentially cause disease.

Warnings

For external use only. If swallowed, get medical help or contact a Poison Control Center immediately.

Keep out of reach of children

Do not use

• in children less than 2 months of age
• on open skin wounds

When using this product keep out of eyes, ears, and mouth. In case of contact with eyes, rinse eyes thoroughly with water. Children must be supervised when using this product.

Stop use and ask a doctor if: irritation or rash occurs. These maybe signs of a serious condition.

Directions

For maximum efficiency, pump the product into wet hands, lather vigorously, sinse and dry.

Inactive Ingredients

Water, Sodium C14-16 Olefin Sulfonate, Cocamidopropyl Betaine, Coco Glucoside, Glycerin, Polysorbate-20, PEG-150 Pentaerythrityl Tetrastearate, PEG-6 Caprylic/Capric Glycerides, Guar Hydroxypropyltrimonium Chloride, Polyquaternium-10, Sodium Hyaluronate, Tocopheryl Acetate, Argania Spinosa Kernel (Argan) Oil, Phenoxyethanol, Ethylhexylglycerin, Citric Acid, Fragrance.

Other Information

Store at room temperature 68°F to 77°F (20° to 25°C)
Do not expose to excessive heat.
You may report a serious adverse reaction to: Hautehouse, LLC, 909 NW Terrace, Fort Lauderdale, FL 33311 USA

For Questions

HAUTEHOUSE INC.
909 NW Terrace
Fort Lauderdale, FL 33311 USA
+1 (954) 376-8966
www.hautehouse.com